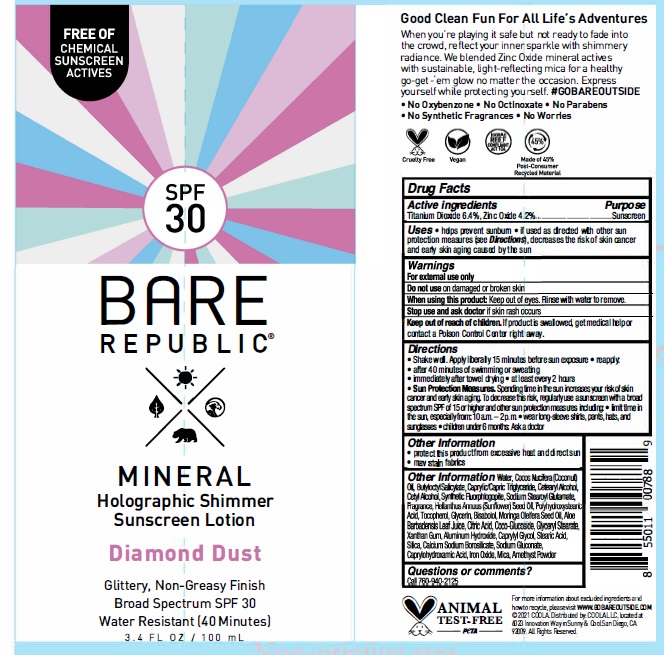 DRUG LABEL: Bare Republic Mineral Shimmer SPF 30 Diamond Dust
NDC: 79753-063 | Form: LOTION
Manufacturer: COOLA, LLC
Category: otc | Type: HUMAN OTC DRUG LABEL
Date: 20240522

ACTIVE INGREDIENTS: TITANIUM DIOXIDE 6.4 g/100 mL; ZINC OXIDE 4.2 g/100 mL
INACTIVE INGREDIENTS: POLYHYDROXYSTEARIC ACID (2300 MW); TOCOPHEROL; XANTHAN GUM; STEARIC ACID; SILICON DIOXIDE; CALCIUM ALUMINUM BOROSILICATE; MICA; WATER; FERRIC OXIDE RED; MORINGA OLEIFERA SEED OIL; ALUMINUM HYDROXIDE; CAPRYLHYDROXAMIC ACID; CETOSTEARYL ALCOHOL; MAGNESIUM POTASSIUM ALUMINOSILICATE FLUORIDE; COCONUT OIL; ALOE VERA LEAF; SODIUM GLUCONATE; CAPRYLYL GLYCOL; GLYCERIN; CETYL ALCOHOL; CITRIC ACID MONOHYDRATE; GLYCERYL MONOSTEARATE; LEVOMENOL; BUTYLOCTYL SALICYLATE; DISODIUM STEAROYL GLUTAMATE; COCO GLUCOSIDE; SUNFLOWER OIL; STANNIC OXIDE

Bare Republic Mineral Shimmer Lotion SPF 30 - Diamond Dust

ACTIVE INGREDIENT

Titanium Dioxide - 6.4%

Zinc Oxide - 4.2%

PURPOSE

Sunscreen

Uses

- Helps prevent sunburn
- if used as directed with other sun protection measures (see Directions), decreases the risk of skin cancer and early skin aging caused by the sun

WARNINGS

- For external use only
- Do not use on damaged or broken skin
- When using this product: Keep out of eyes. Rinse with water to remove.
- Stop use and ask doctor if skin rash occurs

Keep out of reach of children. If swallowed, get medical help or contact a Poison Control Center right away.

Directions

- Shake well. Apply liberally 15 minutes before sun exposure
- Reapply: • After 40 minutes of swimming or sweating • Immediately after towel drying • At least every 2 hours
- Sun Protection Measures. Spending time in the sun increases your risk of skin cancer and early skin aging. To decrease this risk, regularly use a sunscreen with a broad spectrum SPF of 15 or higher and other sun protection measures including: • limit time in the sun, especially from: 10 a.m. – 2 p.m. • wear long-sleeve shirts, pants, hats, and sunglasses
- Children under 6 months: Ask a doctor

OTHER SAFETY INFORMATION

- Protect this product from excessive heat and direct sun

INACTIVE INGREDIENT

Water, Cocos Nucifera (Coconut) Oil, Butyloctyl Salicylate, Caprylic/Capric Triglyceride, Cetearyl Alcohol, Cetyl Alcohol, Synthetic Fluorphlogopite, Sodium Stearoyl Glutamate, Fragrance, Helianthus Annuus (Sunflower) Seed Oil, Polyhydroxystearic Acid, Tocopherol, Glycerin, Tocopherol, Moringa Oleifera Seed Oil, Aloe Barbadensis Leaf Juice, Citric Acid, Coco-Glucoside, Glyceryl Stearate, Xanthan Gum, Aluminum Hydroxide, Caprylyl Glycol, Stearic Acid, Silica, Calcium Sodium Borosilicate, Sodium Gluconate, Caprylhydroxamic Acid, Iron Oxides, Mica, Amethyst Powder

QUESTIONS

Call 760-940-2125